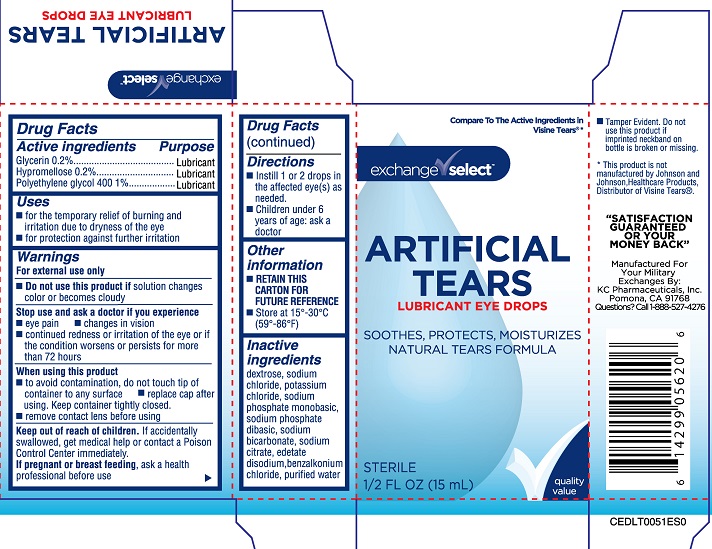 DRUG LABEL: Exchange Select Artificial Tears Lubricant Eye Drops
NDC: 55301-178 | Form: SOLUTION
Manufacturer: Army and Air Force Exchange Service
Category: otc | Type: HUMAN OTC DRUG LABEL
Date: 20251230

ACTIVE INGREDIENTS: POLYETHYLENE GLYCOL 400 1 g/100 mL; HYPROMELLOSE, UNSPECIFIED 0.2 g/100 mL; GLYCERIN 0.2 g/100 mL
INACTIVE INGREDIENTS: DEXTROSE; SODIUM CHLORIDE; SODIUM PHOSPHATE, MONOBASIC; SODIUM PHOSPHATE, DIBASIC; SODIUM CITRATE; BENZALKONIUM CHLORIDE; WATER; POTASSIUM CHLORIDE; SODIUM BICARBONATE; EDETATE DISODIUM

Exchange Select Artificial Tears (PLD)

Active ingredients

Glycerin 0.2%

Hypromellose 0.2%

Polyethylene glycol 400 1%

Purpose

Glycerin....Lubricant

Hypromellose....Lubricant

Polyethylene glycol 400....Lubricant

Uses

- For temporary relief of burning and irritation due to dryness of the eye
- for protection against further irritation

Warnings

For external use only

Do not use this product if solution changes color or becomes cloudy

Stop use and ask a doctor if you experience

- eye pain
- changes in vision
- continued redness or irritation of the eye or if the condition worsens or persists for more than 72 hours

When using this product

- to avoid contamination, do not touch tip of container to any surface
- replace cap after using. Keep container tightly closed.
- remove contact lens bvefore using

Keep out of reach of children. If accidentally swallowed, get medical help or contact a Poison Control Center immediately.

PREGNANCY OR BREAST FEEDING

If pregnant or breast feeding, ask a health professional before use

Directions

- Instill 1 or 2 drops in the affected eye(s) as needed.
- Children under 6 years of age: ask a doctor

Other information

- RETAIN THIS CARTON FOR FUTURE REFERENCE
- Store at 15º-30ºC (59º-86ºF)

Inactive ingredients

dextrose, sodium chloride, potassium chloride, sodium phosphate monobasic, sodium phosphate dibasic, sodium bicarbonate, sodium citrate, edetate disodium, benzalkonium chloride, purified water.